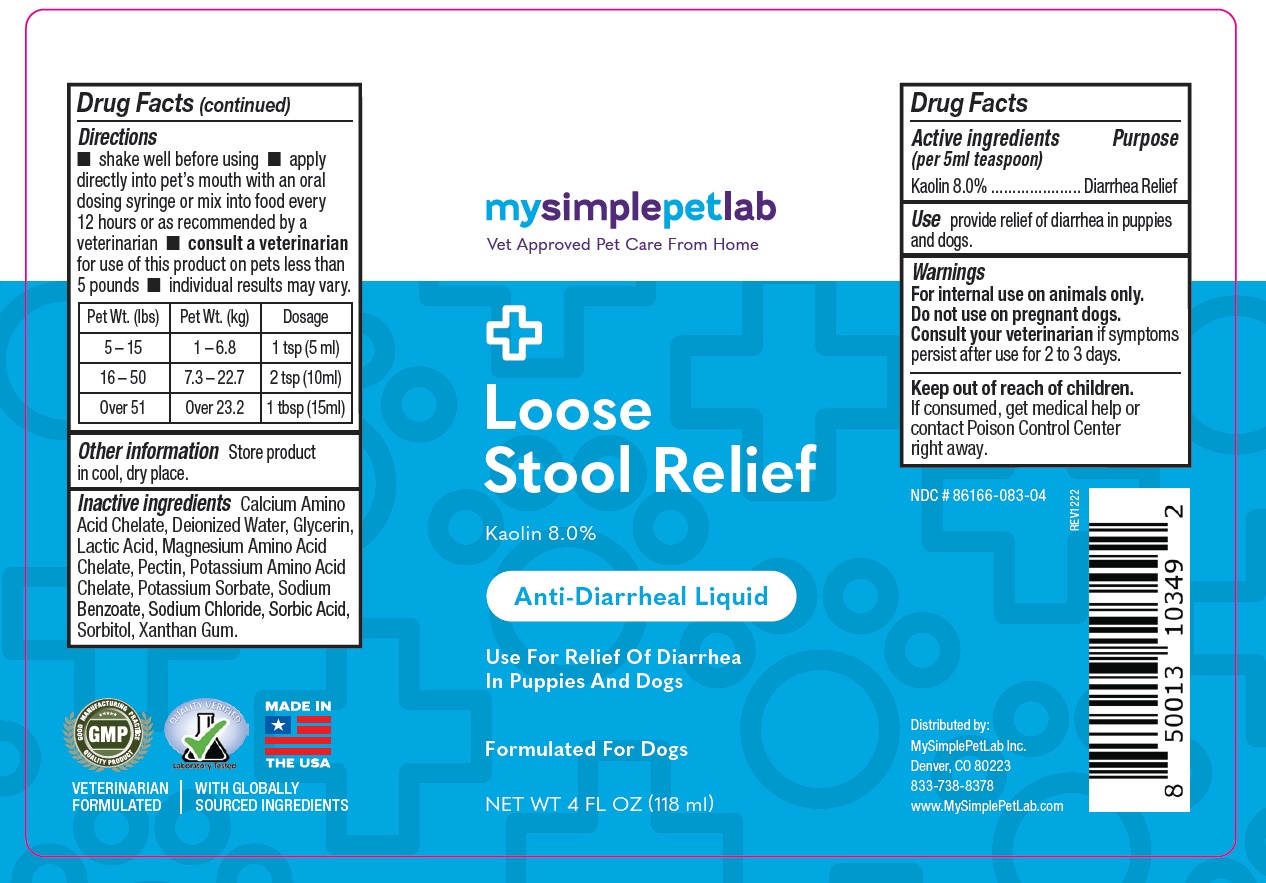 DRUG LABEL: MySimplePetLab Loose Stool Relief
NDC: 86166-083 | Form: LIQUID
Manufacturer: Mysimplepetlab Inc
Category: animal | Type: OTC ANIMAL DRUG LABEL
Date: 20221205

ACTIVE INGREDIENTS: KAOLIN 8 g/100 mL
INACTIVE INGREDIENTS: CALCIUM; WATER; GLYCERIN; LACTIC ACID, UNSPECIFIED FORM; MAGNESIUM; PECTIN; POTASSIUM; POTASSIUM SORBATE; SODIUM BENZOATE; SODIUM CHLORIDE; SORBIC ACID; SORBITOL; XANTHAN GUM

mysimplepetlab Loose Stool Relief

Active ingredients (per 5 ml teaspoon)

Kaolin 8.0%

Purpose

Diarrhea Relief

Use

Provide relief of diarrhea in puppies and dogs.

Warnings

For internal use on animals only.

Do not use on pregnant dogs.

Consult your veterinarian if symptoms persist after use for 2 to 3 days.

Keep out of reach of children.
If consumed, get medical help or contact Poison Control Center right away.

Directions

• shake well before using • apply directly into pet's mouth with an oral dosing syringe or mix into food every 12 hours or as recommended by a veterinarian • consult a veterinarian for use of this product on pets less than 5 pounds • individual results may vary.

Pet Wt. (lbs) | Pet Wt. (kg) | Dosage
5 – 15 | 1 – 6.8 | 1 tsp (5 ml)
16 – 50 | 7.3 – 22.7 | 2 tsp (10ml)
Over 51 | Over 23.2 | 1 tbsp (15ml)

Other information

Store product in cool, dry place.

Inactive ingredients

Calcium Amino Acid Chelate, Deionized Water, Glycerin, Lactic Acid, Magnesium Amino Acid Chelate, Pectin, Potassium Amino Acid Chelate, Potassium Sorbate, Sodium Benzoate, Sodium Chloride, Sorbic Acid, Sorbitol, Xanthan Gum.

Vet Approved Pet Care From Home

Anti-Diarrheal Liquid

Use For Relief of Diarrhea In Puppies And Dogs

Formulated For Dogs

MADE IN THE USA

VETERINARIAN FORMULATED | WITH GLOBALLY SOURCED INGREDIENTS

Distributed by:
MySimplePetLab Inc.
Denver, CO 80223
833-738-8378
www.MySimplePetLab.com